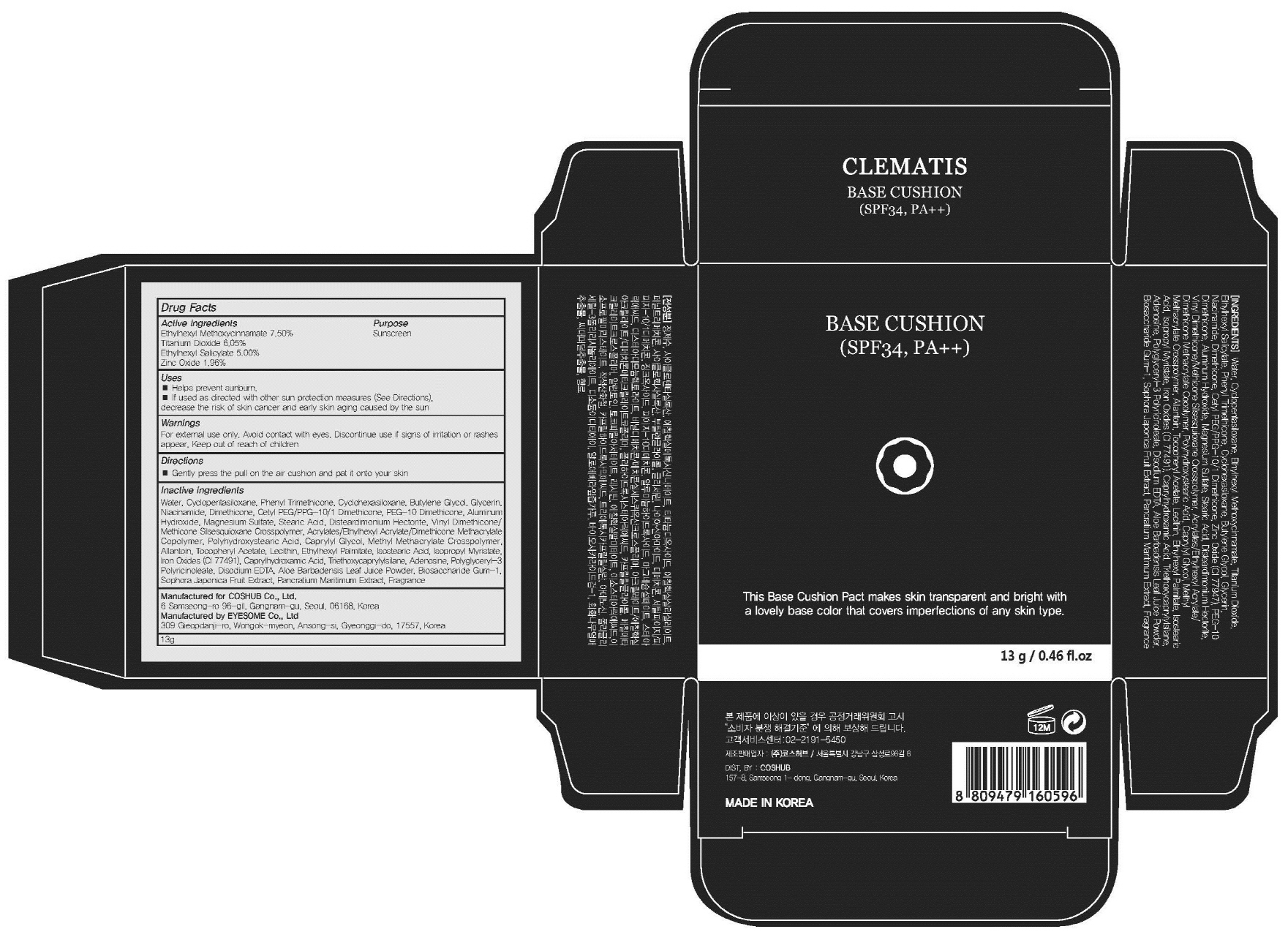 DRUG LABEL: CLEMATIS BASE CUSHION
NDC: 71702-010 | Form: POWDER
Manufacturer: Coshub Co., Ltd.
Category: otc | Type: HUMAN OTC DRUG LABEL
Date: 20170904

ACTIVE INGREDIENTS: Octinoxate 0.97 g/13 g; Titanium Dioxide 0.78 g/13 g; Octisalate 0.65 g/13 g; Zinc Oxide 0.25 g/13 g
INACTIVE INGREDIENTS: Water; Phenyl Trimethicone

ACTIVE INGREDIENT

Active ingredients: Ethylhexyl Methoxycinnamate 7.50%, Titanium Dioxide 6.05%, Ethylhexyl Salicylate 5.00%, Zinc Oxide 1.96%

INACTIVE INGREDIENT

Inactive ingredients: Water, Cyclopentasiloxane, Phenyl Trimethicone, Cyclohexasiloxane, Butylene Glycol, Glycerin, Niacinamide, Dimethicone, Cetyl PEG/PPG-10/1 Dimethicone,PEG-10 Dimethicone, Aluminum Hydroxide, Magnesium Sulfate, Stearic Acid, Disteardimonium Hectorite, Vinyl Dimethicone/Methicone Silsesquioxane Crosspolymer, Acrylates/Ethylhexyl Acrylate/Dimethicone Methacrylate Copolymer, Polyhydroxystearic Acid , Caprylyl Glycol, Methyl Methacrylate Crosspolymer, Allantoin, Tocopheryl Acetate, Lecithin, Ethylhexyl Palmitate, Isostearic Acid, Isopropyl Myristate, Iron Oxides (CI 77491), Caprylhydroxamic Acid, Triethoxycaprylylsilane, Adenosine, Polyglyceryl-3 Polyricinoleate, Disodium EDTA, Aloe Barbadensis Leaf Juice Powder, Biosaccharide Gum-1, Sophora Japonica Fruit Extract, Pancratium Maritimum Extract, Fragrance

PURPOSE

Purpose: Sunscreen

WARNINGS

Warnings: For external use only. Avoid contact with eyes. Discontinue use if signs of irritation or rashes appear. Keep out of reach of children.

DESCRIPTION

Uses: - Helps prevent sunburn. - If used as directed with other sun protection measures (See Directions), decrease the risk of skin cancer and early skin aging caused by the sun

Directions: Gently press the pull on the air cushion and pat it onto your skin